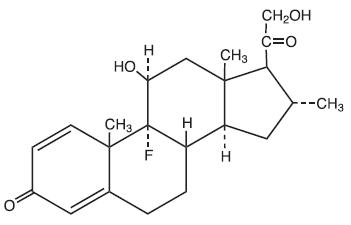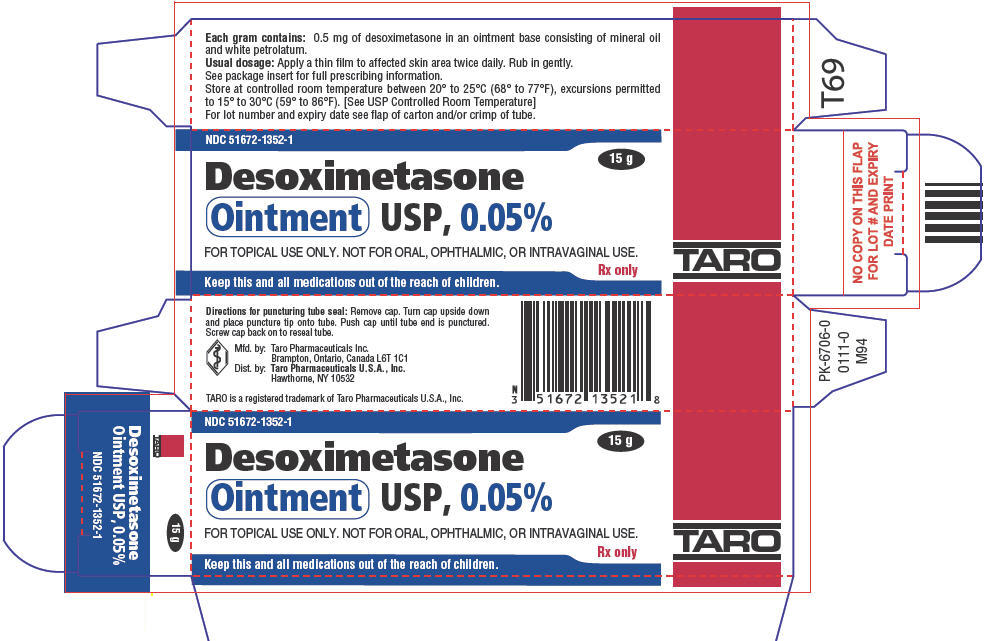 DRUG LABEL: Desoximetasone
NDC: 51672-1352 | Form: OINTMENT
Manufacturer: Sun Pharmaceutical Industries, Inc.
Category: prescription | Type: HUMAN PRESCRIPTION DRUG LABEL
Date: 20250703

ACTIVE INGREDIENTS: DESOXIMETASONE 0.5 mg/1 g
INACTIVE INGREDIENTS: MINERAL OIL; PETROLATUM

Desoximetasone
Ointment USP, 0.05%

For topical use only. Not for oral, ophthalmic, or intravaginal use.

Rx only

DESCRIPTION

Desoximetasone ointment USP, 0.05% contains the active synthetic corticosteroid desoximetasone.

The topical corticosteroids constitute a class of primarily synthetic steroids used as anti-inflammatory and antipruritic agents.

Each gram of desoximetasone ointment USP, 0.05% contains 0.5 mg of desoximetasone in an ointment base consisting of mineral oil and white petrolatum.

The chemical name of desoximetasone is Pregna-1, 4-diene-3, 20-dione, 9-fluoro-11, 21-dihydroxy-16-methyl-,(11β,16α)-.

Desoximetasone has the molecular formula C22H29FO4and a molecular weight of 376.47. The CAS Registry Number is 382-67-2.

The structural formula is:

CLINICAL PHARMACOLOGY

Topical corticosteroids share anti-inflammatory, antipruritic and vasoconstrictive actions.

The mechanism of anti-inflammatory activity of the topical corticosteroids is unclear. Various laboratory methods, including vasoconstrictor assays, are used to compare and predict potencies and/or clinical efficacies of the topical corticosteroids. There is some evidence to suggest that a recognizable correlation exists between vasoconstrictor potency and therapeutic efficacy in man.

Pharmacokinetics

The extent of percutaneous absorption of topical corticosteroids is determined by many factors including the vehicle, the integrity of the epidermal barrier, and the use of occlusive dressings.

Topical corticosteroids can be absorbed from normal intact skin. Inflammation and/or other disease processes in the skin increase percutaneous absorption. Occlusive dressings substantially increase the percutaneous absorption of topical corticosteroids. Thus, occlusive dressings may be a valuable therapeutic adjunct for treatment of resistant dermatoses.

Once absorbed through the skin, topical corticosteroids are handled through pharmacokinetic pathways similar to systemically administered corticosteroids. Corticosteroids are bound to plasma proteins in varying degrees. Corticosteroids are metabolized primarily in the liver and are then excreted by the kidneys. Some of the topical corticosteroids and their metabolites are also excreted into the bile.

Pharmacokinetic studies in men with desoximetasone ointment USP, 0.25% with tagged desoximetasone showed no detectable level (limit of sensitivity: 0.003 µg/mL) in 1 subject and 0.004 and 0.006 µg/mL in the remaining 2 subjects in the blood when it was applied topically on the back followed by occlusion for 24 hours. The extent of absorption for the ointment was 7% based on radioactivity recovered from urine and feces. Seven days after application, no further radioactivity was detected in urine or feces. Studies with other similarly structured steroids have shown that predominant metabolite reaction occurs through conjugation to form the glucuronide and sulfate ester.

INDICATIONS AND USAGE

Desoximetasone ointment USP, 0.05% is indicated for the relief of the inflammatory and pruritic manifestations of corticosteroid-responsive dermatoses.

CONTRAINDICATIONS

Desoximetasone ointment USP, 0.05% is contraindicated in those patients with a history of hypersensitivity to any of the components of the preparation.

WARNINGS

Keep out of reach of children.

PRECAUTIONS

General

Systemic absorption of topical corticosteroids can produce reversible hypothalamic-pituitary-adrenal (HPA) axis suppression with the potential for clinical glucocorticosteroid insufficiency. This may occur during treatment or upon withdrawal of the topical corticosteroid.

Because of the potential for systemic absorption, use of topical corticosteroids may require that patients be periodically evaluated for HPA axis suppression. Factors that predispose a patient using a topical corticosteroid to HPA axis suppression include the use of more potent steroids, use over large surface areas, use over prolonged periods, use under occlusion, use on an altered skin barrier, and use in patients with liver failure.

An ACTH stimulation test may be helpful in evaluating patients for HPA axis suppression. If HPA axis suppression is documented, an attempt should be made to gradually withdraw the drug, to reduce the frequency of application, or to substitute a less potent steroid. Manifestations of adrenal insufficiency may require supplemental systemic corticosteroids. Recovery of HPA axis function is generally prompt and complete upon discontinuation of topical corticosteroids.

Cushing's syndrome, hyperglycemia, and unmasking of latent diabetes mellitus can also result from systemic absorption of topical corticosteroids.

Use of more than one corticosteroid-containing product at the same time may increase the total systemic corticosteroid exposure.

Pediatric patients may be more susceptible to systemic toxicity from use of topical corticosteroids.

Local Adverse Reactions with Topical Corticosteroids

Local adverse reactions may be more likely to occur with occlusive use, prolonged use or use of higher potency corticosteroids. Reactions may include atrophy, striae, telangiectasias, burning, itching, irritation, dryness, folliculitis, acneiform eruptions, hypopigmentation, perioral dermatitis, allergic contact dermatitis, secondary infection, and miliaria. Some local adverse reactions may be irreversible.

Allergic Contact Dermatitis with Topical Corticosteroids

Allergic contact dermatitis to any component of topical corticosteroids is usually diagnosed by a failure to heal rather than a clinical exacerbation. Clinical diagnosis of allergic contact dermatitis can be confirmed by patch testing.

Concomitant skin infections should be treated with an appropriate antimicrobial agent.

If the infection persists, desoximetasone ointment USP, 0.05% should be discontinued until the infection has been adequately treated.

Information for the Patient

Patients using topical corticosteroids should receive the following information and instructions:

1. This medication is to be used as directed by the physician. It is for external use only. Avoid contact with the eyes.
2. Patients should be advised not to use this medication for any disorder other than that for which it was prescribed.
3. The treated skin area should not be bandaged or otherwise covered or wrapped so as to be occlusive unless directed by the physician.
4. Patients should report any signs of local adverse reactions, especially under occlusive dressings.
5. Other corticosteroid-containing products should not be used with desoximetasone ointment USP, 0.05% without first consulting with the physician.

As with other corticosteroids, therapy should be discontinued when control is achieved. If no improvement is seen within 4 weeks, contact the physician.

Laboratory Tests

The following tests may be helpful in evaluating the hypothalamic-pituitary-adrenal (HPA) axis suppression:

- Urinary free cortisol test
- ACTH stimulation test

Carcinogenesis, Mutagenesis, and Impairment of Fertility

Long-term animal studies have not been performed to evaluate the carcinogenic potential or the effect on fertility of topical corticosteroids.

Desoximetasone was nonmutagenic in the Ames test.

Pregnancy

Teratogenic Effects

Pregnancy Category C

Corticosteroids have been shown to be teratogenic in laboratory animals when administered systemically at relatively low dosage levels. Some corticosteroids have been shown to be teratogenic after dermal application in laboratory animals.

Desoximetasone has been shown to be teratogenic and embryotoxic in mice, rats, and rabbits when given by subcutaneous or dermal routes of administration in doses 15 to 150 times the human dose of desoximetasone ointment USP, 0.05%.

There are no adequate and well-controlled studies in pregnant women on teratogenic effects from topically applied corticosteroids. Therefore, desoximetasone ointment USP, 0.05% should be used during pregnancy only if the potential benefit justifies the potential risk to the fetus. Drugs of this class should not be used extensively on pregnant patients, in large amounts, or for prolonged periods of time.

Nursing Mothers

It is not known whether topical administration of corticosteroids could result in sufficient systemic absorption to produce detectable quantities in breast milk. Systemically administered corticosteroids are secreted into breast milk in quantities not likely to have a deleterious effect on the infant. Nevertheless, caution should be exercised when topical corticosteroids are administered to a nursing woman.

Pediatric Use

Pediatric patients may demonstrate greater susceptibility to topical corticosteroid-induced HPA axis suppression and Cushing's syndrome than mature patients because of a larger skin surface area to body weight ratio.

Hypothalamic-pituitary-adrenal (HPA) axis suppression, Cushing's syndrome, and intracranial hypertension have been reported in pediatric patients receiving topical corticosteroids. Manifestations of adrenal suppression in pediatric patients include linear growth retardation, delayed weight gain, low plasma cortisol levels, and absence of response to ACTH stimulation. Manifestations of intracranial hypertension include bulging fontanelles, headaches, and bilateral papilledema.

Administration of topical corticosteroids to pediatric patients should be limited to the least amount compatible with an effective therapeutic regimen. Chronic corticosteroid therapy may interfere with the growth and development of pediatric patients.

ADVERSE REACTIONS

The following local adverse reactions are reported infrequently with topical corticosteroids, but may occur more frequently with the use of occlusive dressings. These reactions are listed in an approximate decreasing order of occurrence:

Burning, itching, irritation, dryness, folliculitis, hypertrichosis, acneiform eruptions, hypopigmentation, perioral dermatitis, allergic contact dermatitis, maceration of the skin, secondary infection, skin atrophy, striae, and miliaria.

In controlled clinical studies the incidence of adverse reactions was low (0.2%) for desoximetasone ointment USP, 0.05% and included mild burning sensation at the site of application.

OVERDOSAGE

Topically applied corticosteroids can be absorbed in sufficient amounts to produce systemic effects (see PRECAUTIONS).

DOSAGE AND ADMINISTRATION

Apply a thin film of desoximetasone ointment USP, 0.05% to the affected skin areas twice daily. Rub in gently.

HOW SUPPLIED

Desoximetasone ointment USP, 0.05% is supplied in:

15 gram (NDC 51672-1352-1), 30 gram (NDC 51672-1352-2), 60 gram (NDC 51672-1352-3) and 100 gram (NDC 51672-1352-7) tubes.

STORAGE AND HANDLING

Store at controlled room temperature between 20° to 25°C (68° to 77°F), excursions permitted to 15° to 30°C (59° to 86°F). [See USP Controlled Room Temperature]

Mfd. by: Taro Pharmaceuticals Inc., Brampton, Ontario, Canada L6T 1C1
Dist. by: Taro Pharmaceuticals U.S.A.,Inc., Hawthorne, NY 10532
Revised: January, 2013

PK-6709-3
57

PRINCIPAL DISPLAY PANEL - 15 g Tube Carton

NDC 51672-1352-1

15 g

Desoximetasone
Ointment USP, 0.05%

FOR TOPICAL USE ONLY. NOT FOR ORAL, OPHTHALMIC, OR INTRAVAGINAL USE.

Rx only

Keep this and all medications out of the reach of children.

TARO